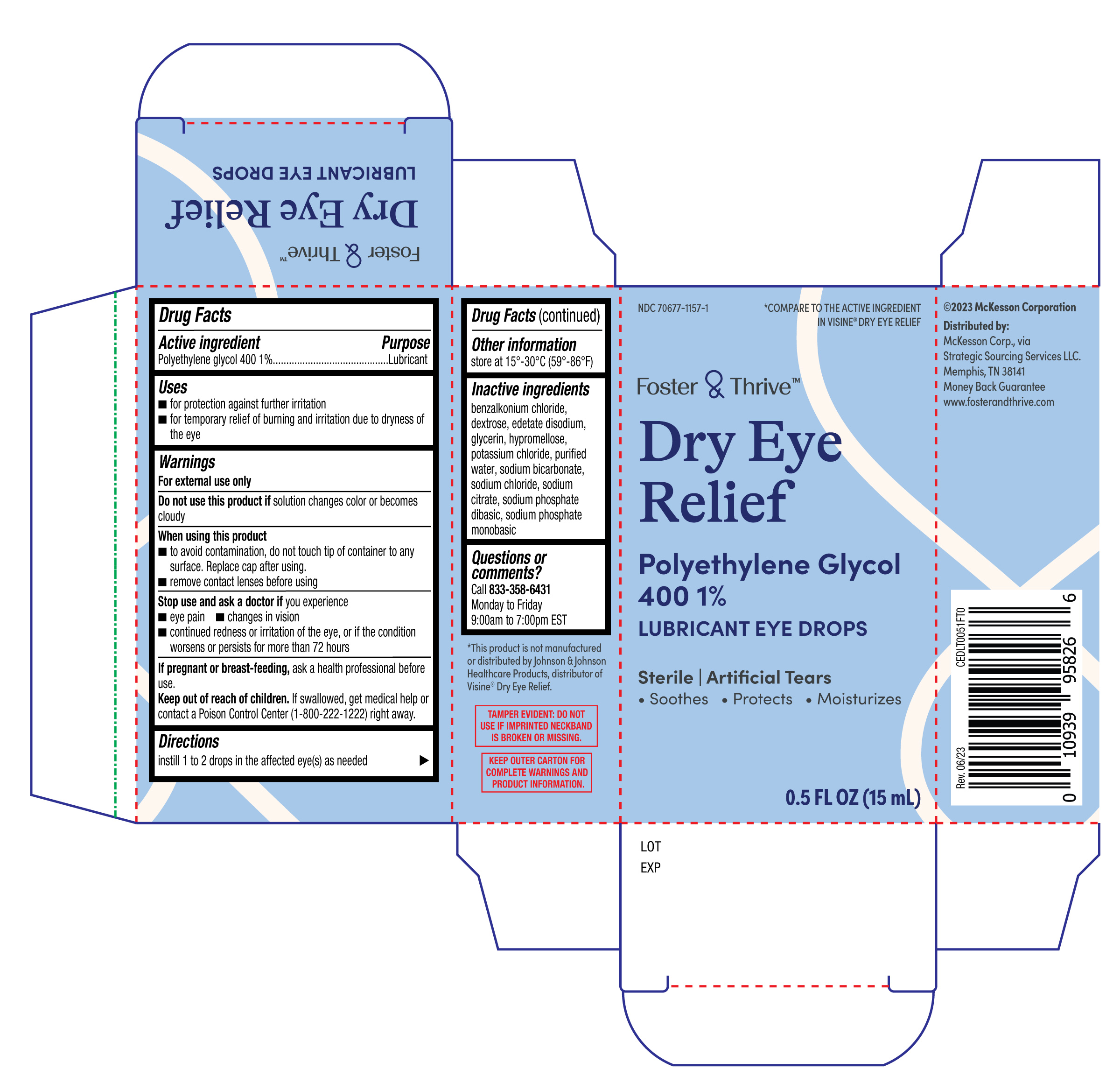 DRUG LABEL: Foster and Thrive Dry Eye Relief
NDC: 70677-1157 | Form: SOLUTION/ DROPS
Manufacturer: Strategic Sourcing Services LLC
Category: otc | Type: HUMAN OTC DRUG LABEL
Date: 20251230

ACTIVE INGREDIENTS: POLYETHYLENE GLYCOL 400 1 g/100 mL
INACTIVE INGREDIENTS: DEXTROSE; WATER; SODIUM PHOSPHATE, DIBASIC; GLYCERIN; HYPROMELLOSE, UNSPECIFIED; SODIUM BICARBONATE; SODIUM PHOSPHATE, MONOBASIC, ANHYDROUS; BENZALKONIUM CHLORIDE; EDETATE DISODIUM; POTASSIUM CHLORIDE; SODIUM CHLORIDE; SODIUM CITRATE

Foster & Thrive Dry Eye Relief 15mL (PLD)

Active ingredient

Polyethylene glycol 400 1%

Purpose

Lubricant

Uses

- for protection against further irritation
- for temporary relief of burning and irritation due to dryness of the eye

Warnings

For external use only

Do not use this product if

solution changes color or becomes cloudy

When using this product

- to avoid contamination, do not touch tip of container to any surface. Replace cap after using.
- remove contact lenses before using

Stop use and ask a doctor if

you experience

- eye pain
- changes in vision
- continued redness or irritation of the eye, or if the condition worsens or persists for more than 72 hours

If pregnant or breast-feeding,

ask a health professional before use.

Keep out of reach of children.

If swallowed, get medical help or contact a Poison Control Center (1-800-222-1222) right away.

Directions

instill 1 to 2 drops in the affected eye(s) as needed

Other information

store at 15°-30°C (59°-86°F)

Inactive ingredients

benzalkonium chloride, dextrose, edetate disodium, glycerin, hypromellose, potassium chloride, purified water, sodium bicarbonate, sodium chloride, sodium citrate, sodium phosphate dibasic, sodium phosphate monobasic

Questions or comments?

Call 833-358-6431

Monday to Friday

9:00am to 7:00pm EST